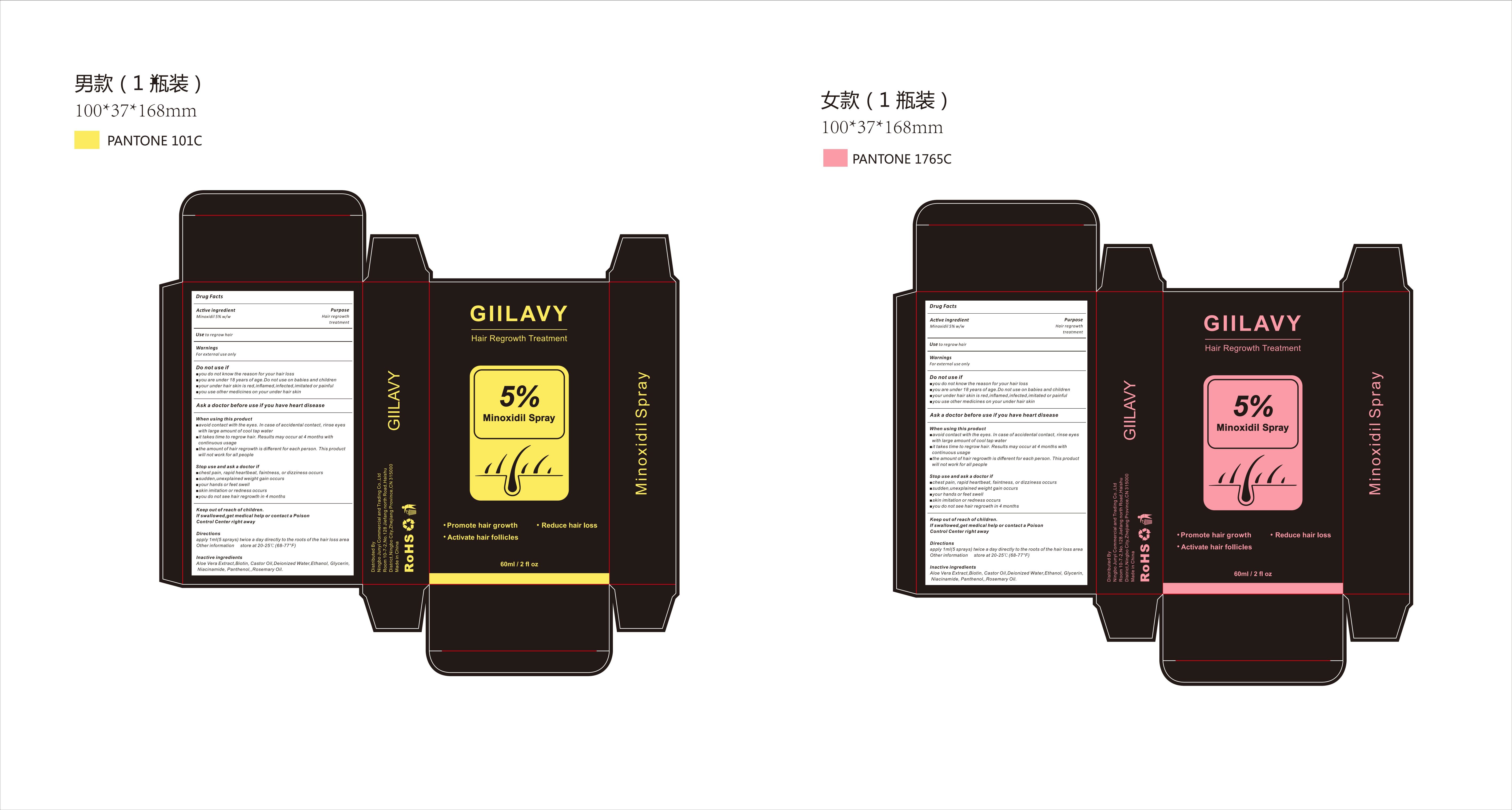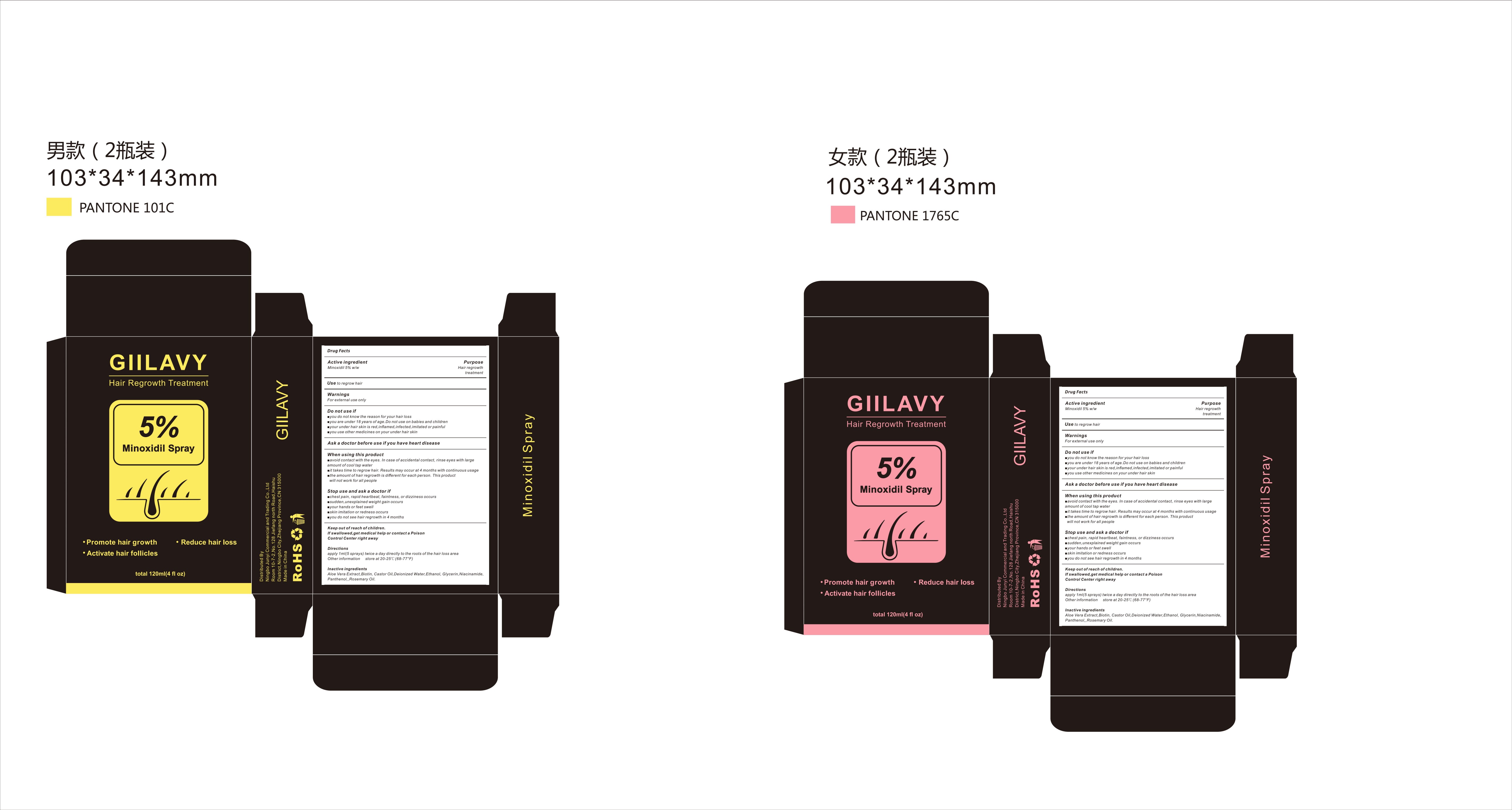 DRUG LABEL: GIILAVY Hair Regrowth Treatment
NDC: 84249-002 | Form: LIQUID
Manufacturer: Ningbo Junyi Trading Co., Ltd
Category: otc | Type: HUMAN OTC DRUG LABEL
Date: 20240425

ACTIVE INGREDIENTS: MINOXIDIL 5 g/100 mL
INACTIVE INGREDIENTS: CASTOR OIL; ALCOHOL; BIOTIN; NIACINAMIDE; WATER; ROSEMARY OIL; ALOE VERA LEAF; GLYCERIN; PANTHENOL

84249-002

Active Ingredient

Minoxidil 5% w/w

Purpose

Hair or beard regrowth treatment

Warnings

For external use only

Do not use

you do not know the reason for your hair or beard loss
you are under 18 years of age.Do not use on babies and children
your under hair or beard skin is red,inflamed,infected,imitated or painful
you use other medicines on your under hair or beard skin

When Using

do not apply on other parts of the body, except the hair or beard
avoid contact with the eyes. In case of accidental contact, rinse eyes with large amount of cool tap water
it takes time to regrow hair. Results may occur at 4 months with continuous usage
the amount of hair or beard regrowth is different for each person. This product will not work for all men

Stop Use

chest pain, rapid heartbeat, faintness, or dizziness occurs
sudden,unexplained weight gain occurs
your hands or feet swell
skin imitation or redness occurs
you do not see hair or beard regrowth in 4 months

Ask Doctor

chest pain, rapid heartbeat, faintness, or dizziness occurs
sudden,unexplained weight gain occurs
your hands or feet swell
skin imitation or redness occurs
you do not see hair or beard regrowth in 4 months

Keep Oot Of Reach Of Children

If swallowed,get medical help or contact a Poison Control Center right away

Directions

apply 1ml(5 sprays) twice a day directly to the roots of the hair or beard loss area

Other information

store at 20-25℃(68-77°F)

Inactive ingredients

Aloe Vera Extract,Biotin, Castor Oil,Deionized Water,Ethanol, Glycerin, Niacinamide, Panthenol,,Rosemary Oil.